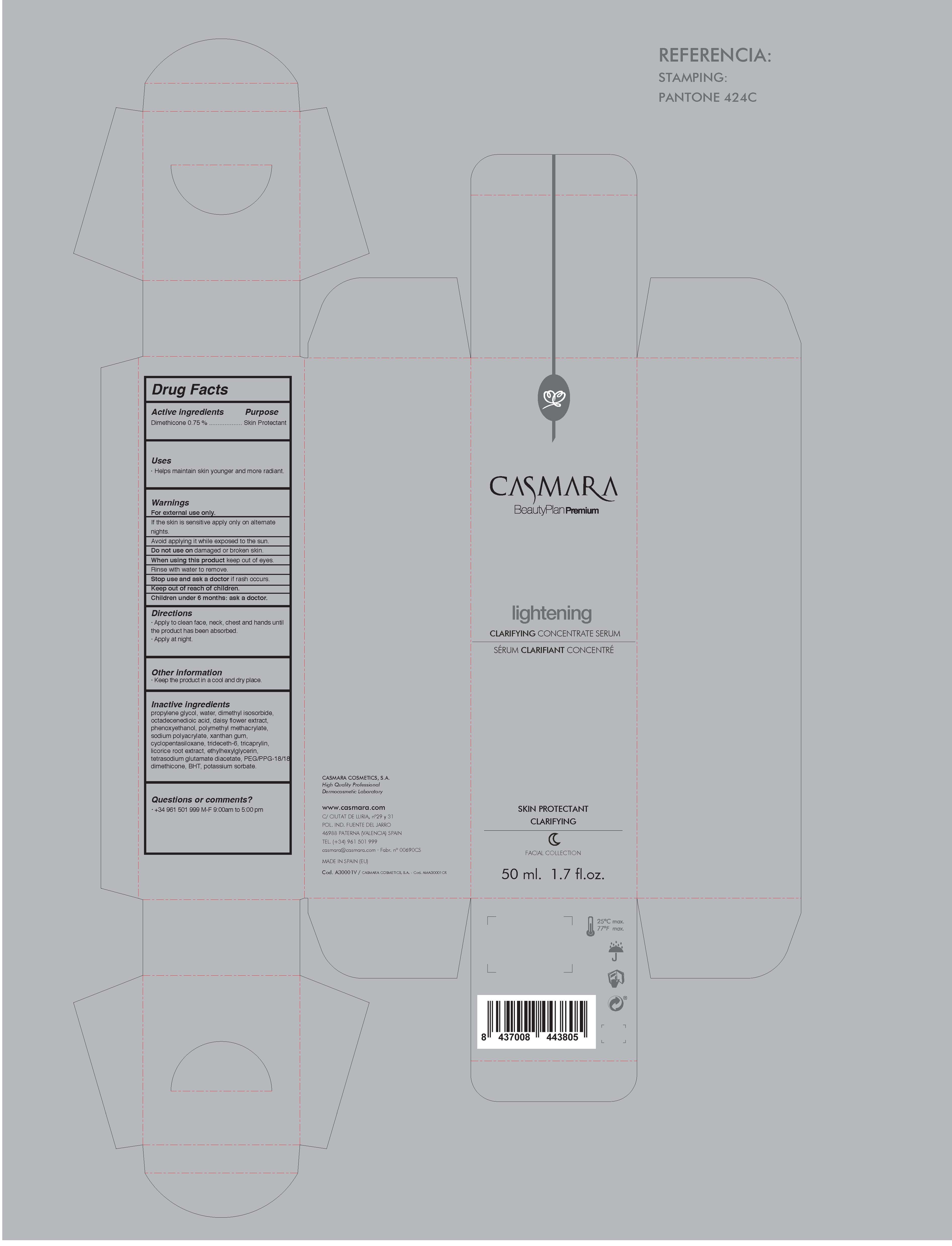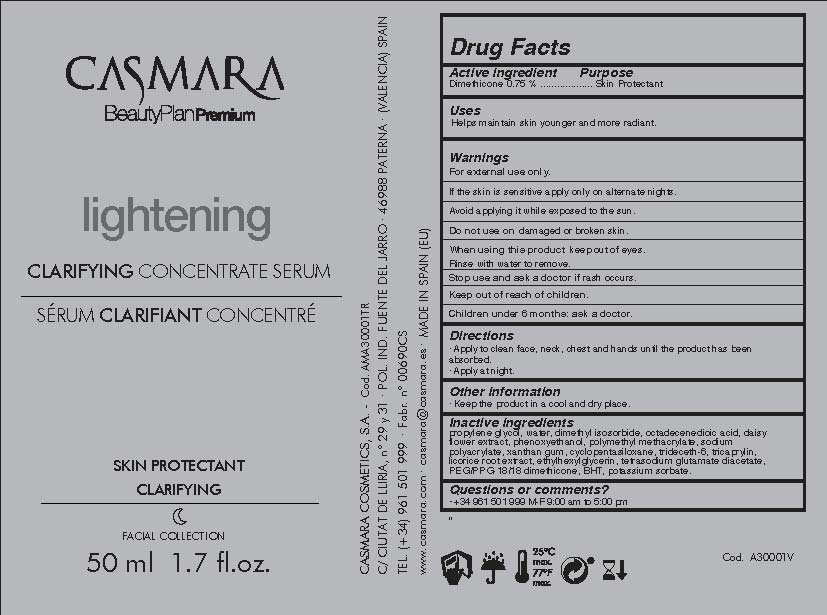 DRUG LABEL: Lightening Clarifying Concentrated Serum
NDC: 20151-103 | Form: CREAM
Manufacturer: Casmara Cosmetics, SA
Category: otc | Type: HUMAN OTC DRUG LABEL
Date: 20170406

ACTIVE INGREDIENTS: DIMETHICONE 0.75 mg/1 mL
INACTIVE INGREDIENTS: XANTHAN GUM 0.5 mg/1 mL; PEG/PPG-18/18 DIMETHICONE 0.09 mg/1 mL; DIMETHYL ISOSORBIDE 3 mg/1 mL; POTASSIUM SORBATE 0.0075 mg/1 mL; OCTADECENEDIOIC ACID 2 mg/1 mL; ETHYLHEXYLGLYCERIN 0.1 mg/1 mL; WATER 48.935 mg/1 mL; PHENOXYETHANOL 0.9 mg/1 mL; TETRASODIUM GLUTAMATE DIACETATE 0.094 mg/1 mL; TRICAPRYLIN 0.21 mg/1 mL; TRIDECETH-6 0.225 mg/1 mL; BUTYLATED HYDROXYTOLUENE 0.052 mg/1 mL; POLY(METHYL METHACRYLATE; 450000 MW) 0.828 mg/1 mL; BELLIS PERENNIS FLOWER 1.5 mg/1 mL; PROPANEDIOL 46 mg/1 mL; SODIUM POLYACRYLATE (2500000 MW) 0.75 mg/1 mL; LICORICE 0.126 mg/1 mL

Lightening Clarifying concentrated serum

ACTIVE INGREDIENTS PURPOSE

Dimethicone 0.75%.................... Skin Protectant

Warnings

For external use only.

Do not use on damaged or broken skin.

When using this product keep our of the eyes. Rinse with water to remove.

Stop use and ask a doctor if rash occurs.

Keep out of reach of children.

Whhen using this product do not get into eyes.

Children under 6 months: as a doctor.

WARNINGS

Stop use and ask a doctor if rash occurs

Children under 6 months: ask a doctor

Warnings

Keep out of reach of children

Questions or comments?

+ 34 961 501 999 M-F 9:00 am to 5:00 pm

Other Information

. keep the product in a cool and dry place

Directions

. apply to clean face, neck and chest and hands until the product has been absorbed.

. apply at night

DOSAGE AND ADMINISTRATION

. apply to clean face, neck and chest and hands until the product has been absorbed.

.apply at night

Uses

. helps maintain skyn younger and more radiant

Inactive Ingredients

Propylene Glycol, Water, Dimethyl Isosorbide, Octadecenedioic Acid, Daisy Flower Extract, Phenoxyethanol, Polymethyl methacrylate, Sodium polyacrylate, Xanthan gum, Cyclopentasiloxane, Trideceth-6, Tricaprylin, Licorice Root Extract, Ethylhexylglycerin, Tetrasodium glutamate diacetate, PEG/PPG-18/18 Dimethicone, BHT, Potassium sorbate

Uses

. helps to maintain the skin younger and more radiant